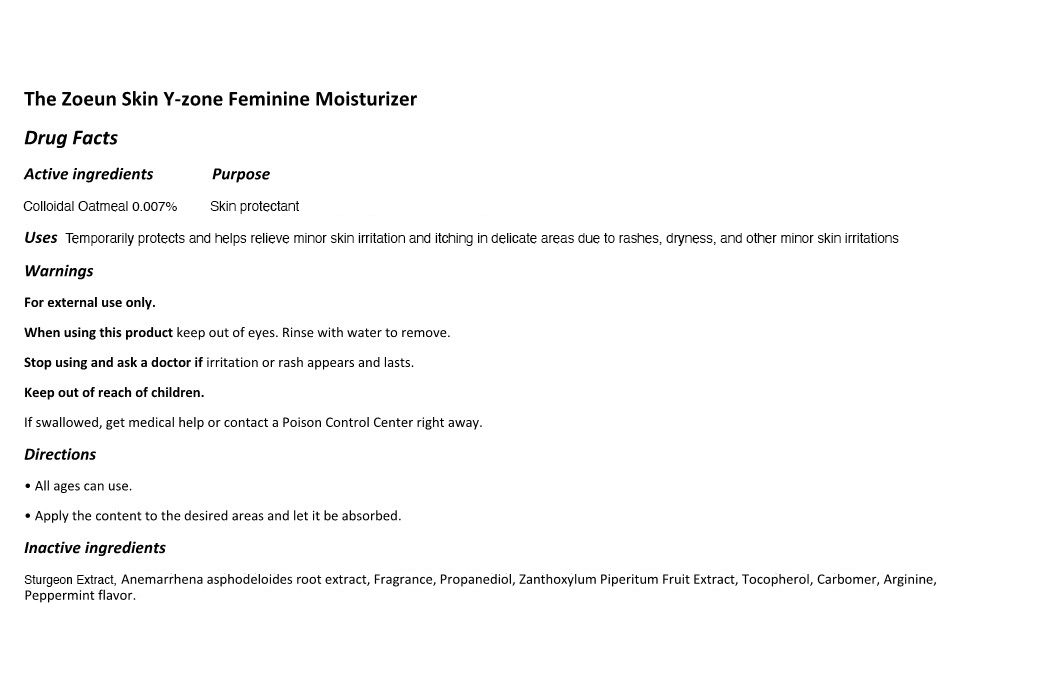 DRUG LABEL: The Zoeun Skin Y-Zone Feminine Moisturizer
NDC: 83636-114 | Form: LIQUID
Manufacturer: Sturgeonbio Co.,Ltd.
Category: otc | Type: HUMAN OTC DRUG LABEL
Date: 20251001

ACTIVE INGREDIENTS: OATMEAL 0.007 g/100 mL
INACTIVE INGREDIENTS: ARGININE; FRAGRANCE 13576; STURGEON, UNSPECIFIED; CARBOMER HOMOPOLYMER, UNSPECIFIED TYPE; ANEMARRHENA ASPHODELOIDES ROOT; PEPPERMINT; PROPANEDIOL; ZANTHOXYLUM PIPERITUM FRUIT PULP; TOCOPHEROL

114 THE ZOEUN SKIN Y-ZONE FEMININE MOISTURIZER

Active Ingredients

Colloidal Oatmeal 0.007%

Purpose

Skin Protectant.

Uses

Temporarily protects and helps relieve minor skin irritation and itching in delicate areas due to rashes, dryness, and other minor skin irritations.

Warnings

For external use only.

Warnings

When using this product keep out of eyes. Rinse with water to remove.

Warnings

Stop using and ask a doctor if irritation or rash appears and lasts.

Directions

• All ages can use.

• Whenever wish to, apply directly to the skin, and let the skin absorb without wiping.

Warnings

Keep out of reach of children.

If swallowed, get medical help or contact a Poison Control Center right away.

Inactive Ingredients

Sturgeon Extract, Anemarrhena asphodeloides root extract, Fragrance, Propanediol, Zanthoxylum Piperitum Fruit Extract, Tocopherol, Carbomer, Arginine, Peppermint flavor.